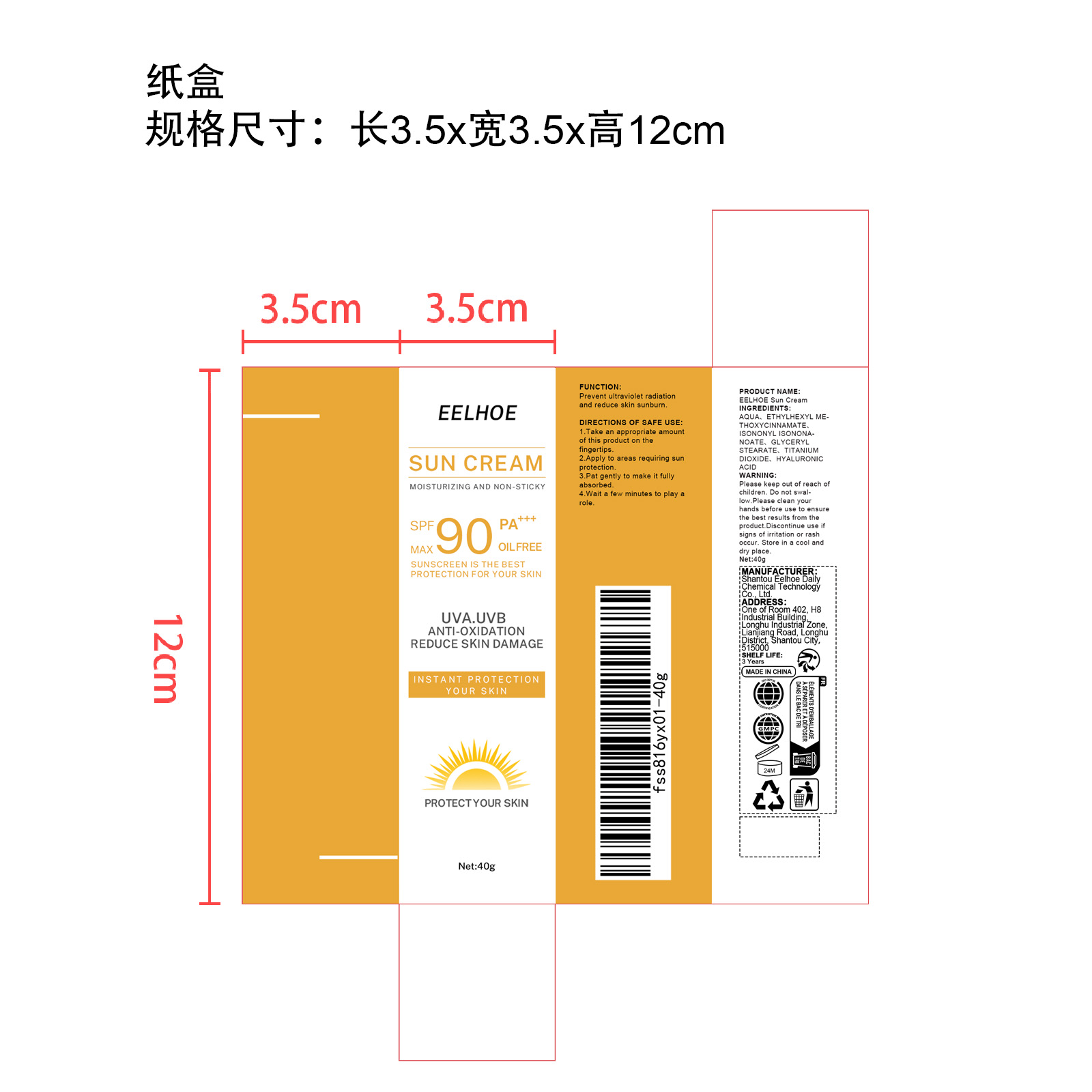 DRUG LABEL: EELHOE Sun Cream
NDC: 85064-004 | Form: CREAM
Manufacturer: Shantou Eelhoe Daily Chemical Technology Co., Ltd.
Category: otc | Type: HUMAN OTC DRUG LABEL
Date: 20251127

ACTIVE INGREDIENTS: CENTELLA ASIATICA TRITERPENOIDS 0.004 mg/40 mg
INACTIVE INGREDIENTS: OCTINOXATE 2 mg/40 mg; GLYCERYL MONOSTEARATE 0.4 mg/40 mg; HYALURONIC ACID 0.004 mg/40 mg; TITANIUM DIOXIDE 0.4 mg/40 mg; ISONONYL ISONONANOATE 1.6 mg/40 mg; AQUA 35.592 mg/40 mg

ACTIVE INGREDIENT

CENTELLA ASIATICA TRITERPENOIDS

PURPOSE

Prevent ultraviolet radiation and reduce skin sunburn.

WHEN USING

1.Take an appropriate amount of this product on the fingertips.

2.Apply to areas requiring sun protection.

3.Pat gently to make it fully absorbed.

4.Wait a few minutes to play a role.

WARNINGS

Please keep out of reach of children. Do not swallow.Please clean your hands before use to ensure the best results from the product. Discontinue use if signs of irritation or rash occur. Store in a cool and dry place.

DO NOT USE

Discontinue use if signs of irritation or rash occur.

STOP USE

Discontinue use if signs of irritation or rash occur.

KEEP OUT OF REACH OF CHILDREN

Please keep out of reach of children. Do not swallow.

STORAGE AND HANDLING

Store in a cool and dry place.

INACTIVE INGREDIENT

AQUA
ETHYLHEXYL METHOXYCINNAMATE
ISONONYL ISONONANOATE
GLYCERYL STEARATE
TITANIUM DIOXIDE
HYALURONIC ACID